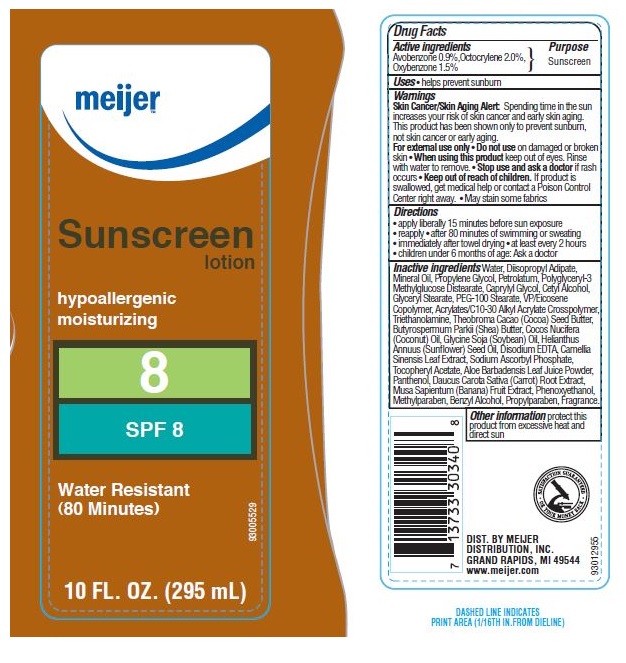 DRUG LABEL: Meijer SPF 8
                        
NDC: 41250-360 | Form: LOTION
Manufacturer: Meijer Distribution Inc
Category: otc | Type: HUMAN OTC DRUG LABEL
Date: 20160519

ACTIVE INGREDIENTS: AVOBENZONE 0.9 g/100 g; OCTOCRYLENE 2 g/100 g; OXYBENZONE 1.5 g/100 g
INACTIVE INGREDIENTS: WATER; DIISOPROPYL ADIPATE; MINERAL OIL; PROPYLENE GLYCOL; PETROLATUM; CAPRYLYL GLYCOL; CETYL ALCOHOL; GLYCERYL MONOSTEARATE; PEG-100 STEARATE; TROLAMINE; COCOA BUTTER; SHEA BUTTER; COCONUT OIL; SOYBEAN OIL; SUNFLOWER OIL; EDETATE DISODIUM; GREEN TEA LEAF; SODIUM ASCORBYL PHOSPHATE; .ALPHA.-TOCOPHEROL ACETATE; ALOE VERA LEAF; BANANA; PHENOXYETHANOL; METHYLPARABEN; BENZYL ALCOHOL; PROPYLPARABEN

Drug Facts

Active Ingredients

AVOBENZONE 0.9%, OCTOCRYLENE 2.0%, OXYBENZONE 1.5%

Purpose

Sunscreen

Uses

helps prevent sunburn

Warnings

Skin Cancer/Skin Aging Alert: Spending time in the sun increases your risk of skin cancer and early skin aging. This product has been shown only to prevent sunburn, not skin cancer or early aging.

For external use only

Do not use

on damaged or broken skin.

When using this product

keep out of eyes. Rinse with water to remove.

Stop use and ask a doctor

if rash occurs.

Keep out of reach of children.

If product is swallowed, get medical help or contact a Poison Control Center right away.

- May stain some fabrics.

Directions

- apply liberally 15 minutes before sun exposure
- reapply
- after 80 minutes of swimming or sweating
- immediately after towel drying
- at least every 2 hours
- children under 6 months of age: Ask a doctor

Inactive ingredients

Water, Diisopropyl Adipate, Mineral Oil, Propylene Glycol, Petrolatum, Polyglyceryl-3 Methylglucose Distearate, Caprylyl Glycol, Cetyl Alcohol, Glyceryl Stearate, PEG-100 Stearate, VP/Eicosene Copolymer, Acrylates/C10-30 Alkyl Acrylate Crosspolymer, Triethanolamine, Theobroma Cacao (Cocoa) Seed Butter, Butyrospermum Parkii (Shea), Butter, Cocos Nucifera (Coconut) Oil, Glycine Soja (Soybean) Oil, Helianthus Annuus (Sunflower) Seed Oil, Disodium EDTA, Camellia Sinensis Leaf Extract, Sodium Ascorbyl Phosphate, Tocopheryl Acetate, Aloe Barbadensis Leaf Juice Powder, Panthenol, Daucus Carota Sativa (Carrot) Root Extract, Musa Sapientum (Banana) Fruit Extract, Phenoxyethanol, Methylparaben, Benzyl Alcohol, Propylparaben, Fragrance.

Other information

protect this product from excessive heat and direct sun

Principal Display Panel

NDC 41250-360-57

meijer

Sunscreen lotion

hypoallergenic

moisturizing

8

SPF 8

Water Resistant

(80 minutes)

10 Fl. Oz. (295 mL)